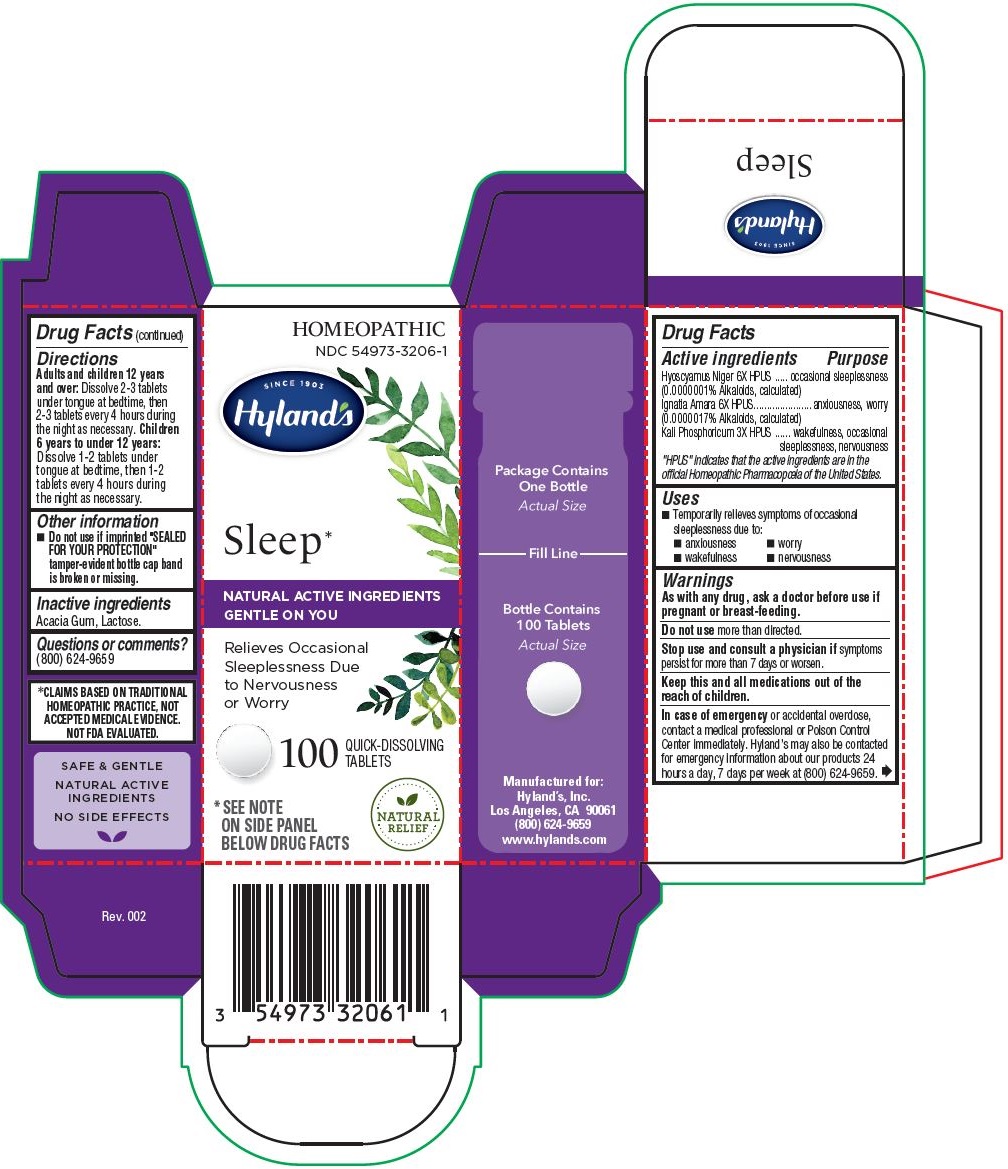 DRUG LABEL: Sleep
NDC: 54973-3206 | Form: TABLET
Manufacturer: Hyland's Inc.
Category: homeopathic | Type: HUMAN OTC DRUG LABEL
Date: 20221214

ACTIVE INGREDIENTS: HYOSCYAMUS NIGER 6 [hp_X]/1 1; STRYCHNOS IGNATII SEED 6 [hp_X]/1 1; POTASSIUM PHOSPHATE, DIBASIC 3 [hp_X]/1 1
INACTIVE INGREDIENTS: ACACIA; LACTOSE

Hyland's Sleep

PURPOSE

Relieves Occasional Sleeplessness Due to Nervousness or Worry

Drug Facts

Active ingredients | Purpose
Hyoscyamus Niger 6X HPUS; (0.0000001% Alkaloids, calculated) | occasional sleeplessness
Ignatia Amara 6X HPUS; (0.0000017% Alkaloids, calculated) | anxiousness, worry
Kali Phosphoricum 3X HPUS | wakefulness, occasional sleeplessness, nervousness

"HPUS" indicates that the active ingredients are in the official Homeopathic Pharmacopoeia of the United States.

Uses

■ Temporarily relieves symptoms of occasional sleeplessness due to:
■ anxiousness ■ worry
■ wakefulness ■ nervousness

Warnings

PREGNANCY OR BREAST FEEDING

As with any drug, ask a doctor before use if pregnant or breast-feeding.

Do not use more than directed.

Stop use and consult a physician if symptoms persist for more than 7 days or worsen.

KEEP OUT OF REACH OF CHILDREN

Keep this and all medications out of the reach of children.

OVERDOSAGE

In case of emergency or accidental overdose, contact a medical professional or Poison Control Center immediately. Hyland’s may also be contacted for emergency information about our products 24 hours a day, 7 days per week at (800) 624-9659.

Drug Facts (continued)

Directions

Adults and children 12 years and over: Dissolve 2-3 tablets under tongue at bedtime, then 2-3 tablets every 4 hours during the night as necessary.

Children 6 years to under 12 years: Dissolve 1-2 tablets under tongue at bedtime, then 1-2 tablets every 4 hours during the night as necessary.

Other information

■ Do not use if imprinted "SEALED FOR YOUR PROTECTION" tamper-evident bottle cap band is broken or missing.

Inactive ingredients

Acacia Gum, Lactose.

Questions or comments?

(800) 624-9659

*CLAIMS BASED ON TRADITIONAL HOMEOPATHIC PRACTICE, NOT ACCEPTED MEDICAL EVIDENCE. NOT FDA EVALUATED.

Indications and Usage

 Temporarily relieves symptoms of occasional
sleeplessness due to:
 anxiousness  worry
 wakefulness  nervousness

Dosage and Administration

Adults and children 12 years and over: Dissolve 2-3 tablets under tongue at bedtime, then 2-3 tablets every 4 hours during the night as necessary.

Children 6 years to under 12 years: Dissolve 1-2 tablets under tongue at bedtime, then 1-2 tablets every 4 hours during the night as necessary.

PRINCIPAL DISPLAY PANEL - 100 Tablet Bottle Carton

HOMEOPATHIC

NDC 54973-3206-1

SINCE 1903

Hyland's

Sleep*

NATURAL ACTIVE INGREDIENTS
GENTLE ON YOU

Relieves Occasional
Sleeplessness Due
to Nervousness
or Worry

100 QUICK-DISSOLVING TABLETS

* SEE NOTE ON SIDE PANEL BELOW DRUG FACTS

NATURAL RELIEF